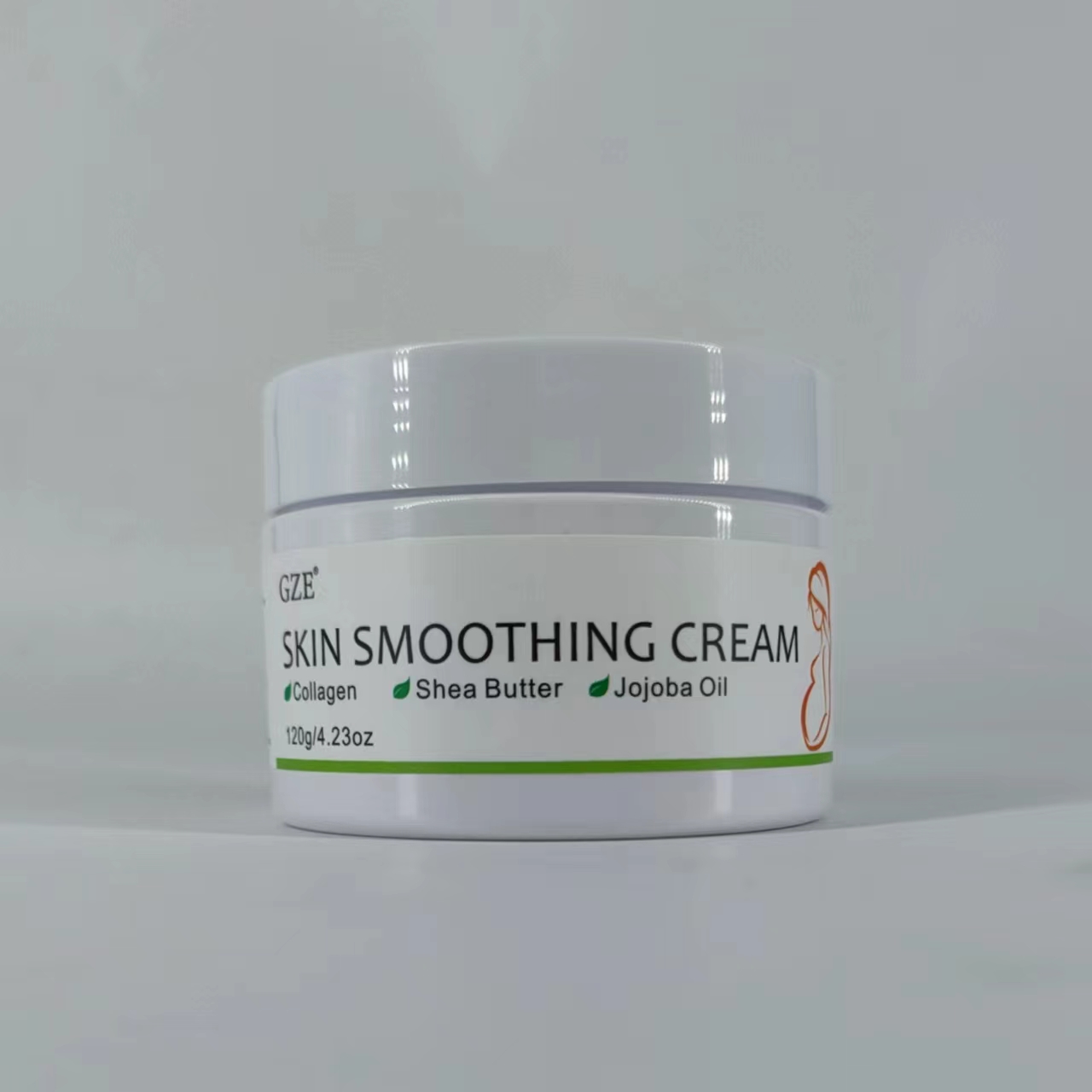 DRUG LABEL: GZE SKIN Smoothing Cream
NDC: 74458-100 | Form: CREAM
Manufacturer: Guangzhou Yilong Cosmetics Co., Ltd
Category: otc | Type: HUMAN OTC DRUG LABEL
Date: 20241108

ACTIVE INGREDIENTS: SALICYLIC ACID 1 g/100 g; ASCORBIC ACID 11.82 g/100 g
INACTIVE INGREDIENTS: HYALURONATE SODIUM; ASCORBYL GLUCOSIDE; LIMNANTHES ALBA (MEADOWFOAM) SEED OIL; SIMMONDSIA CHINENSIS (JOJOBA) SEED OIL; MEDIUM-CHAIN TRIGLYCERIDES; AQUA; CETEARYL ALCOHOL; THEOBROMA CACAO (COCOA) SEED BUTTER; BUTYROSPERMUM PARKII (SHEA) BUTTER; GLYCERIN; COLLAGENASE 3

GZE SKIN SMOOTHING CREAM

ACTIVE INGREDIENT

Ascorbic Acid

Salicylic Acid

INACTIVE INGREDIENT

Aqua

Ascorbyl Glucoside

Diethyl Ascorbic Acid

Hydroxypropyl Cyclodextrin

Glycerin

Sodium Hyaluronate

Limnanthes Alba (Meadowfoam) Seed Oil

Simmondsia Chinensis (Jojoba) Seed Oil

Caprylic/Capric Triglyceride

Theobroma Cacao (Cocoa) Seed Butter

Butyrospermum Parkii (Shea) Butter

Cetearyl Alcohol

PURPOSE

Moisturizing.

INDICATIONS AND USAGE

Apply to the entire skin, focusing on areas prone to problems, such as the abdomen, buttocks, thighs and chest. Massage the skin twice a day.

WARNINGS

For external use only.

Stop use and ask a doctor if rash occurs.

Do not use on damaged or broken skin.

When using this product keep out of eyes. Rinse with water to remove.

Keep out of reach of children. If swallowed, get medical help or contact a Poison Control Center right away.

DOSAGE AND ADMINISTRATION

Apply to the entire skin, focusing on areas prone to problems, such as the abdomen, buttocks, thighs and chest. Massage the skin twice a day.